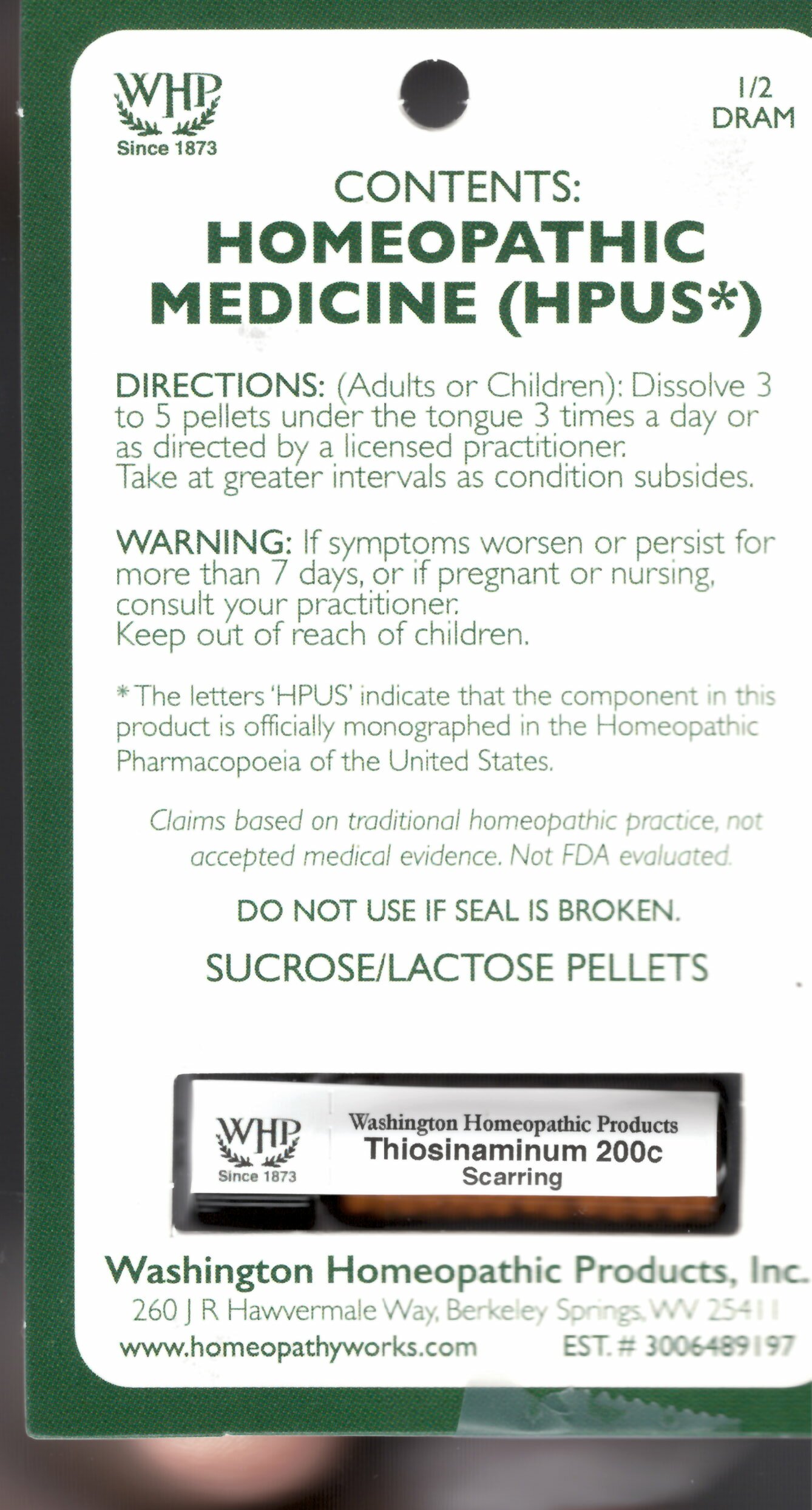 DRUG LABEL: Thiosinaminum
NDC: 71919-820 | Form: PELLET
Manufacturer: Washington Homeopathic Products
Category: homeopathic | Type: HUMAN OTC DRUG LABEL
Date: 20250128

ACTIVE INGREDIENTS: ALLYLTHIOUREA 200 [hp_C]/1 1
INACTIVE INGREDIENTS: SUCROSE; LACTOSE

Thiosinaminum Kit Refill 200c

ACTIVE INGREDIENTS

THIOSINAMINUM 200C

USES

Indicated for Scarring.

KEEP OUT OF REACH OF CHILDREN

As with all medications, keep out of reach of children.

INDICATIONS

THIOSINAMINUM Scarring

STOP USE AND ASK DOCTOR

If symptoms persist or recur, discontinue use. If pregnant or nursing, consult a licensed practitioner before using this product.

DIRECTIONS

(Adults or Children): Dissolve 3 to 5 pellets under tongue 3 times a day or as directed by a licensed practitioner. Take at greater intervals as condition subsides.

INACTIVE INGREDIENTS

Sucrose/Lactose